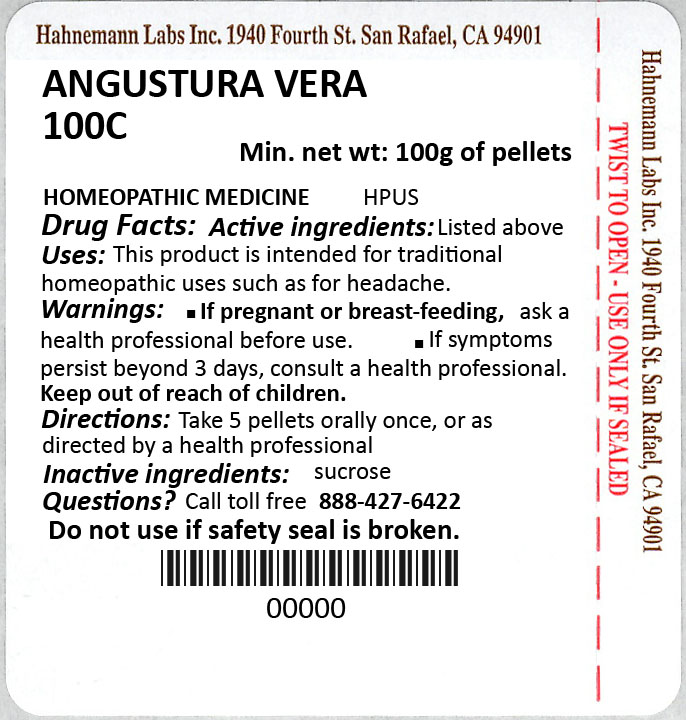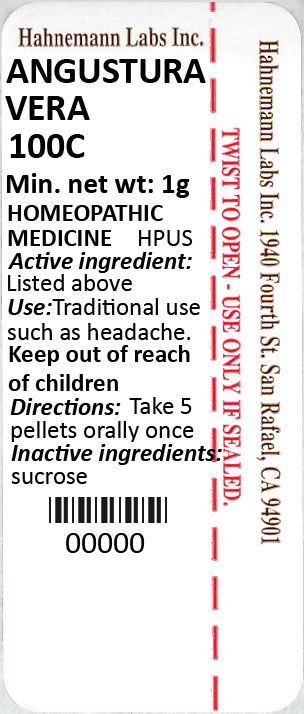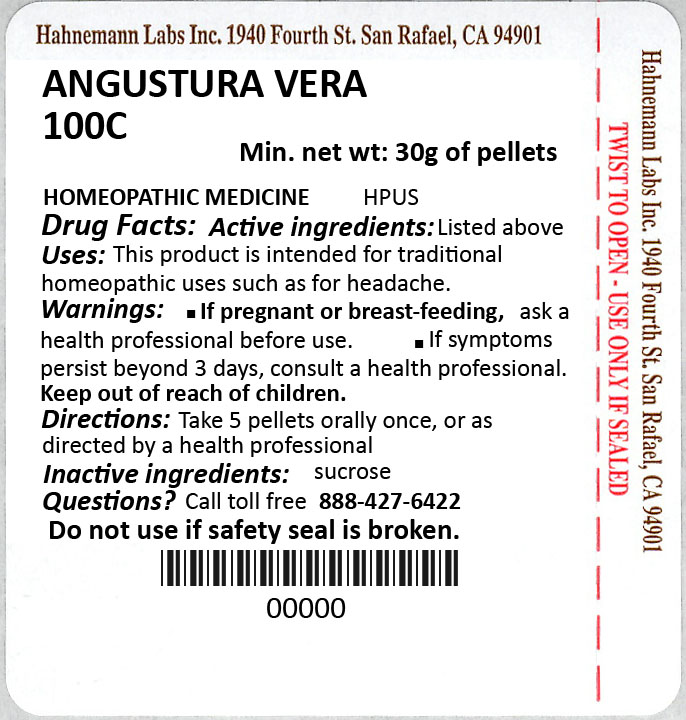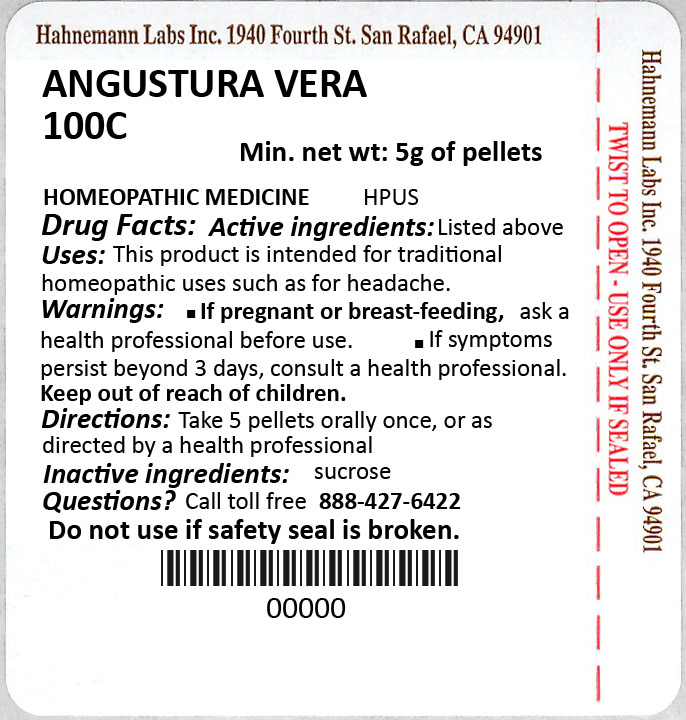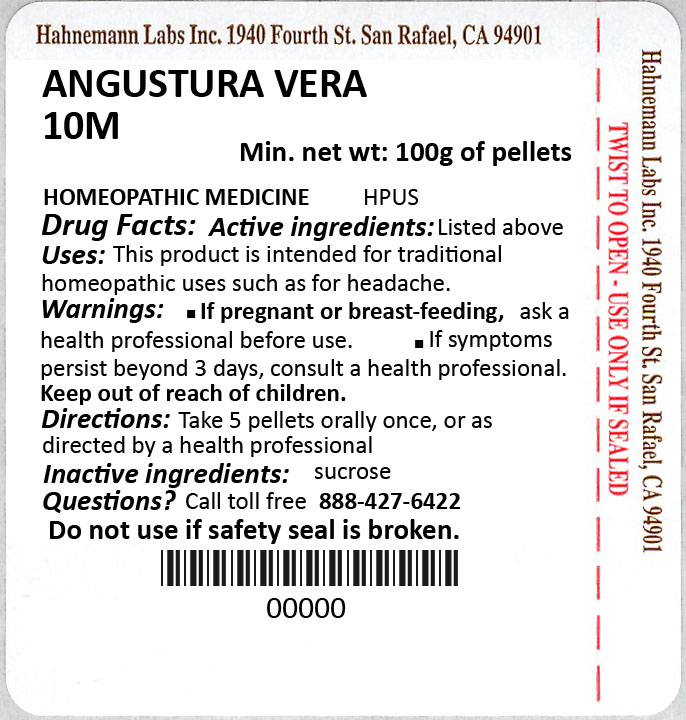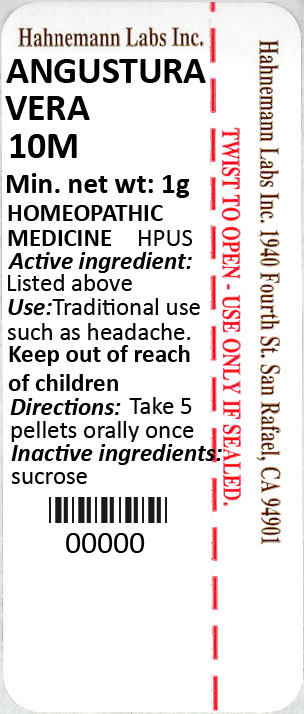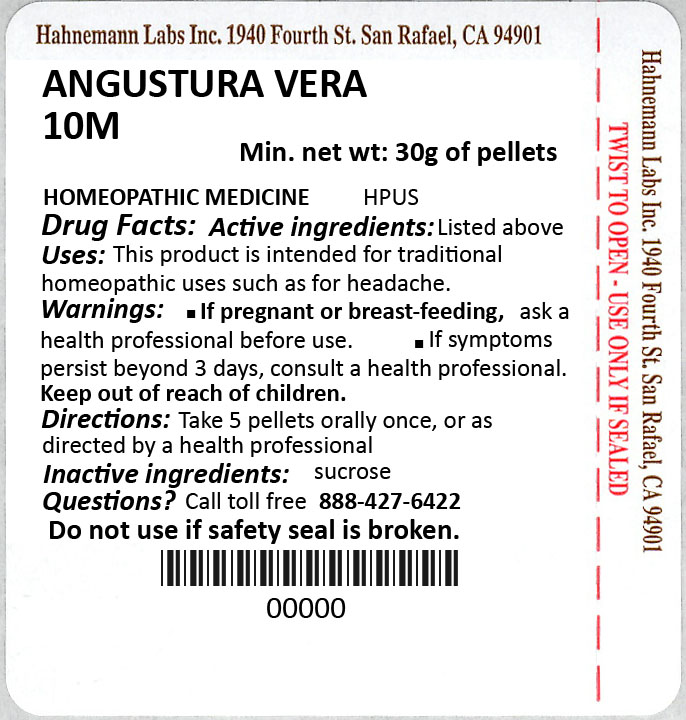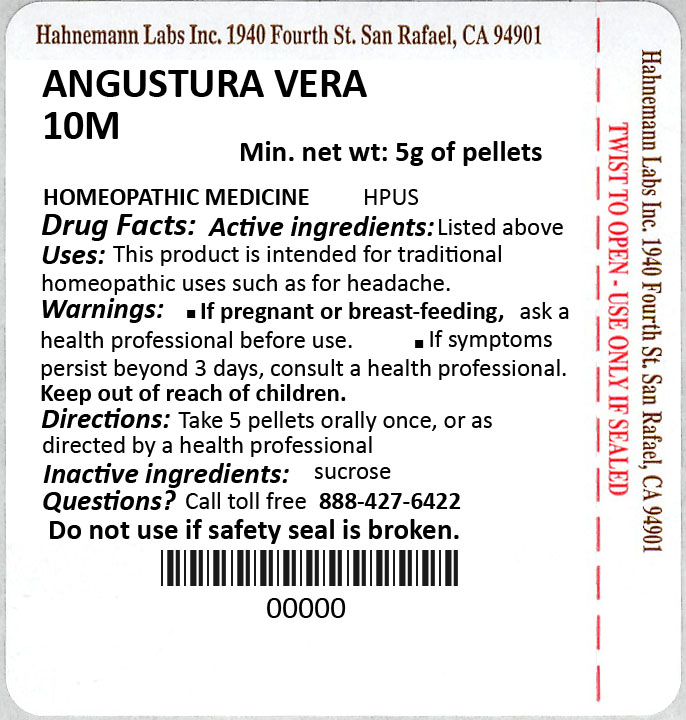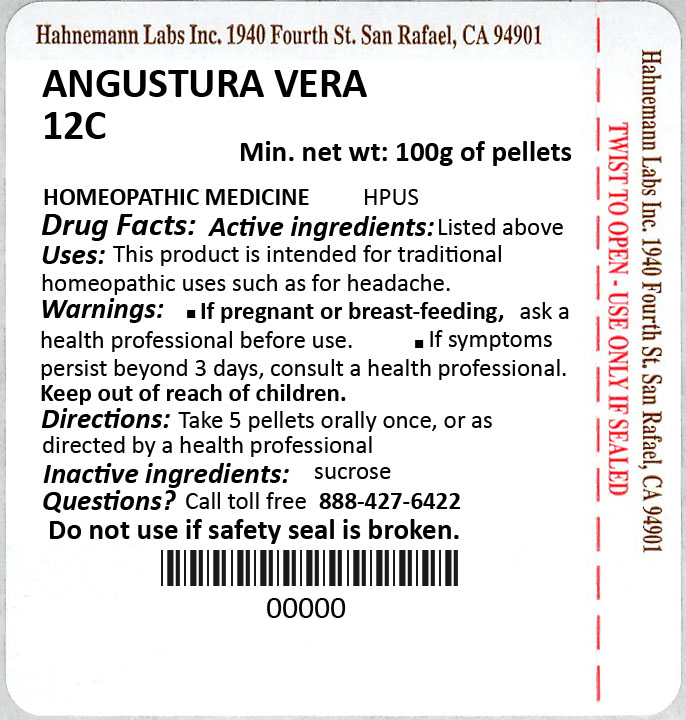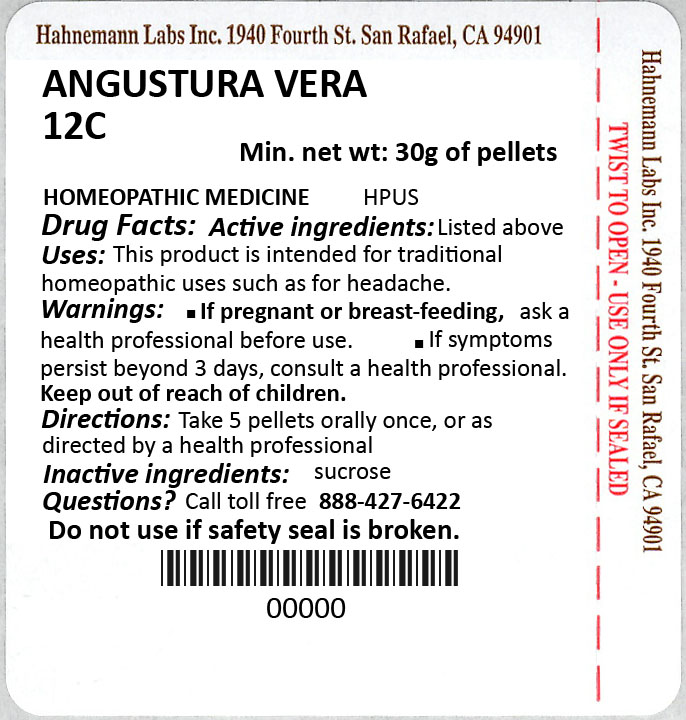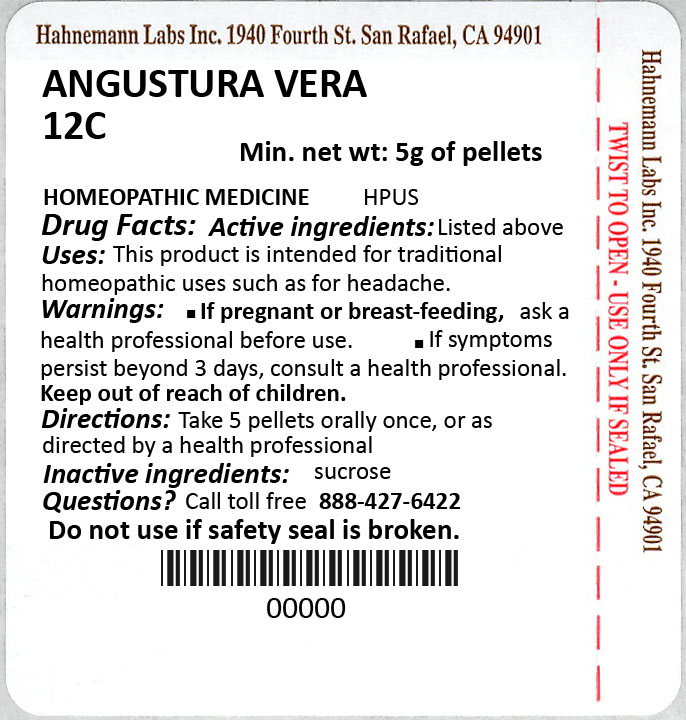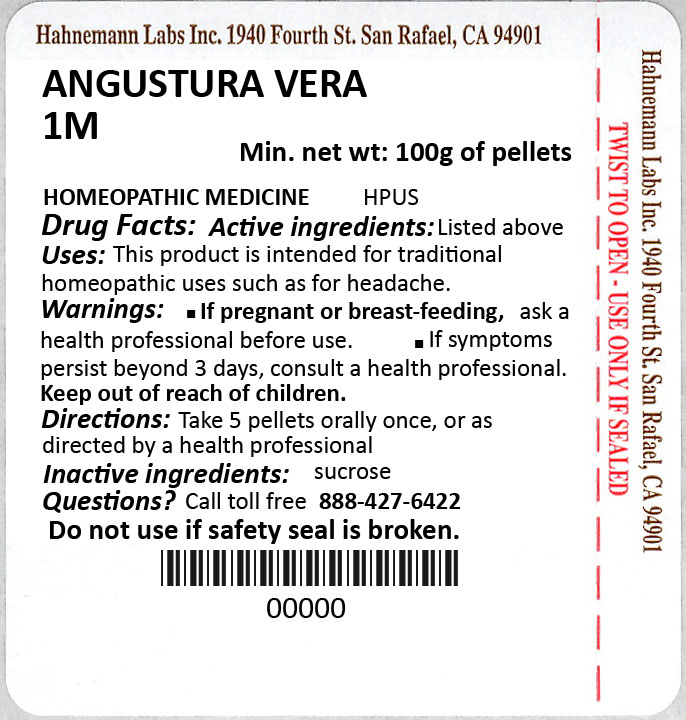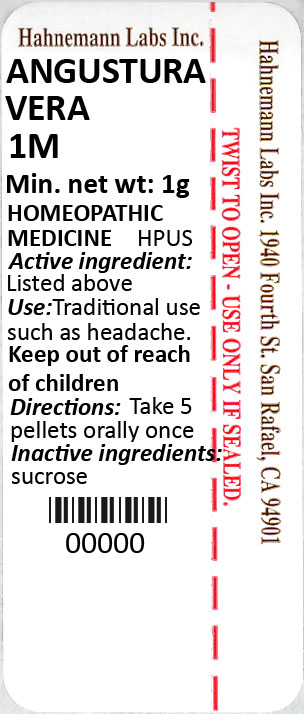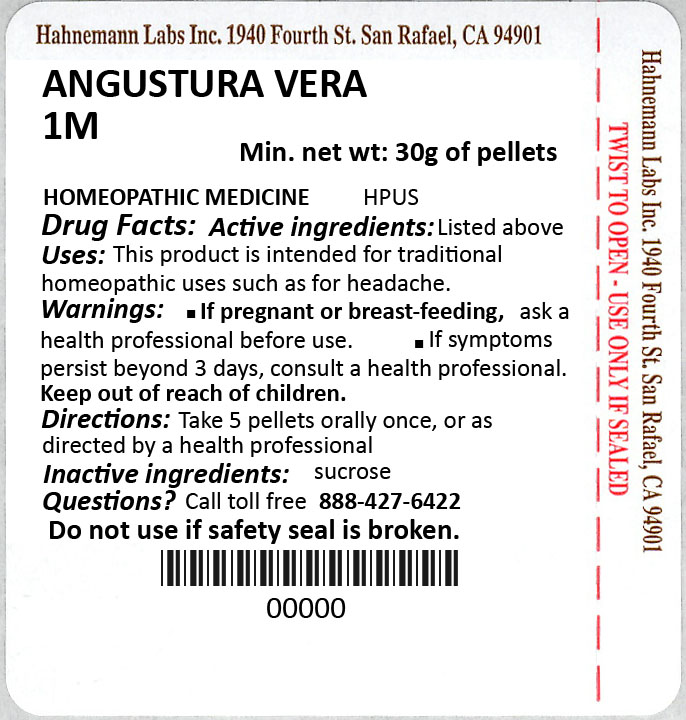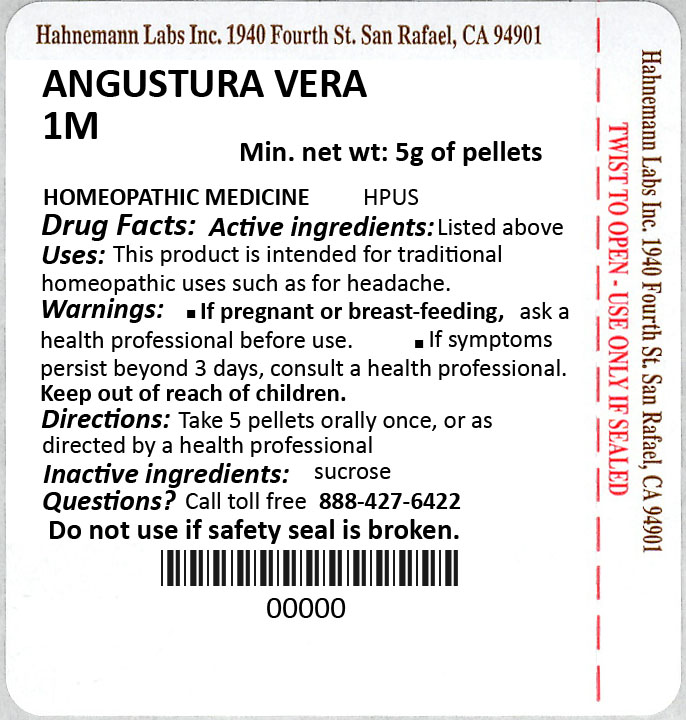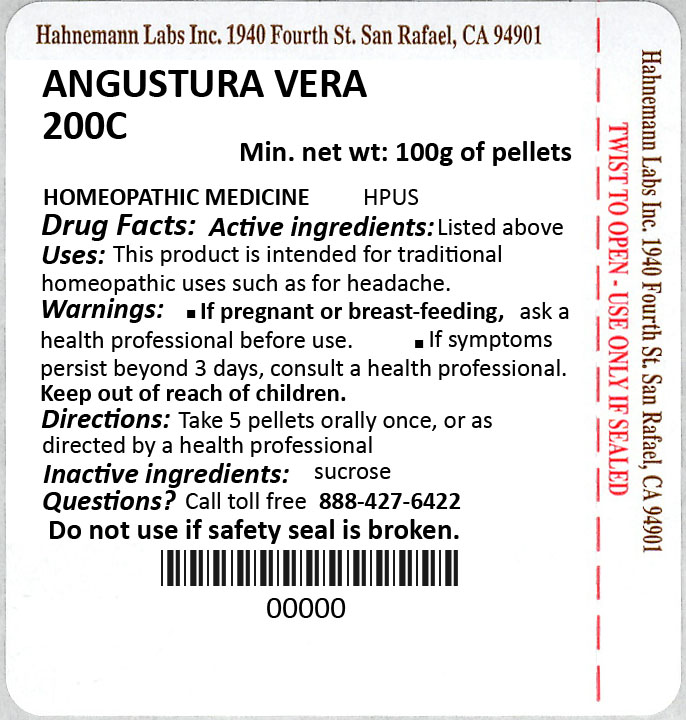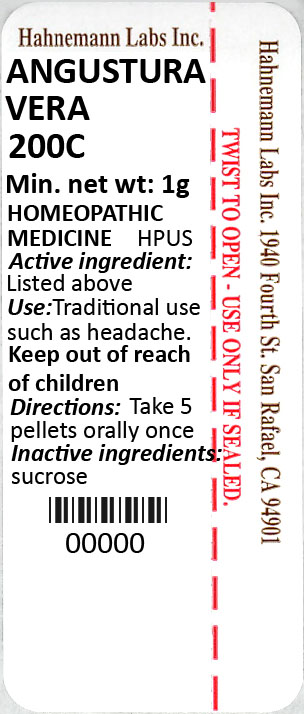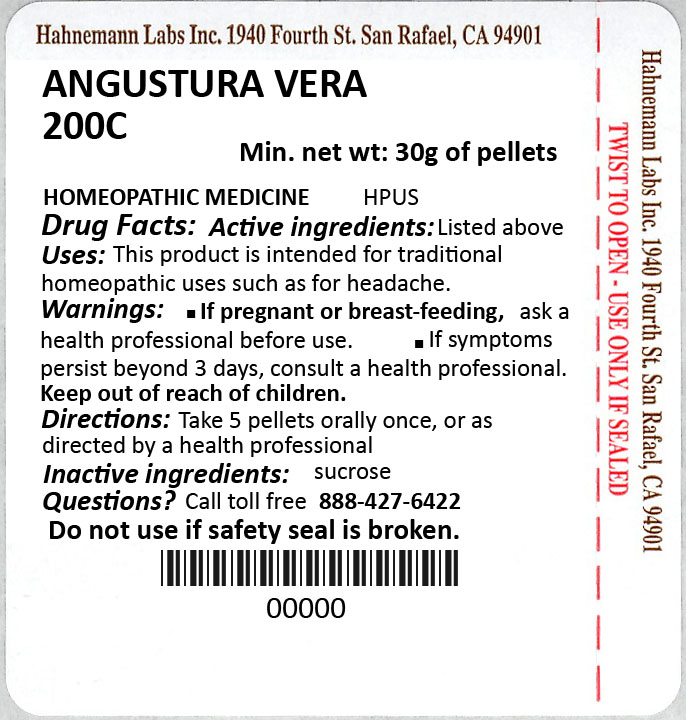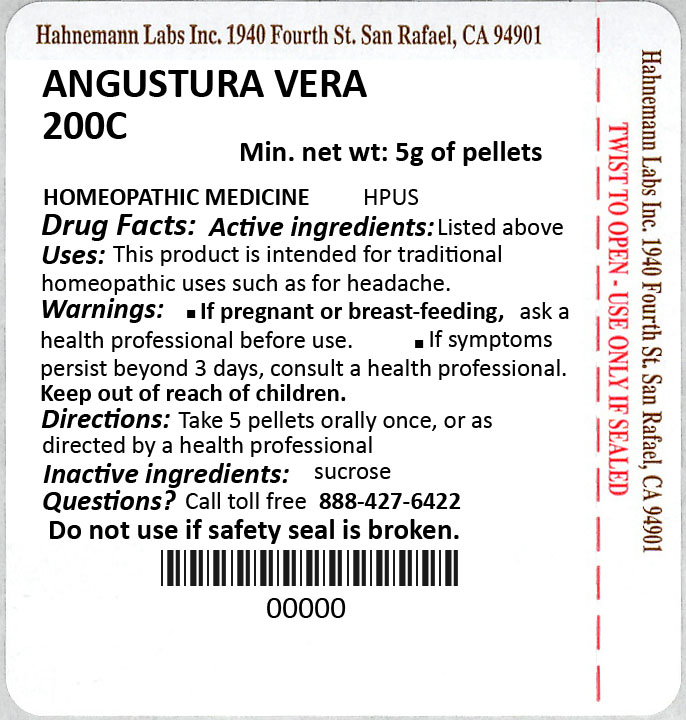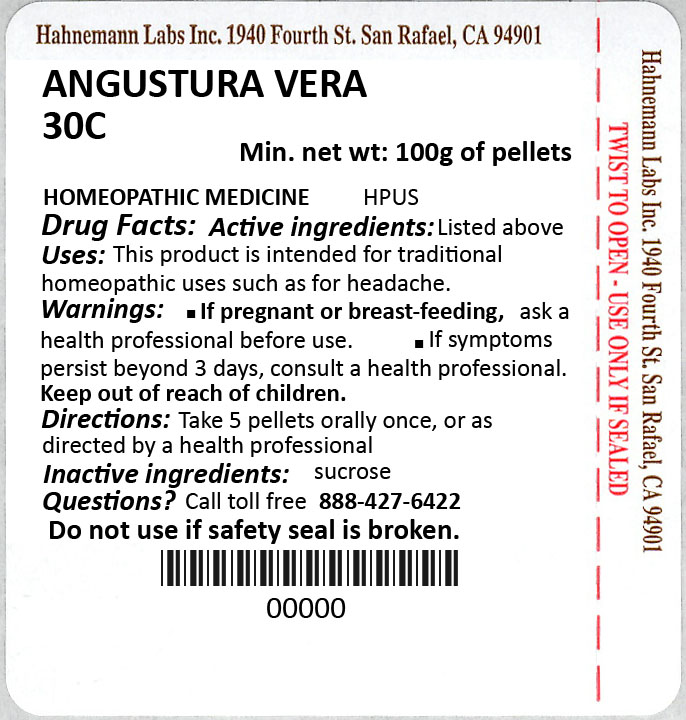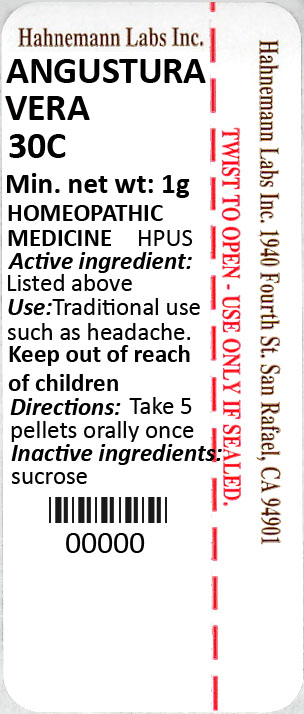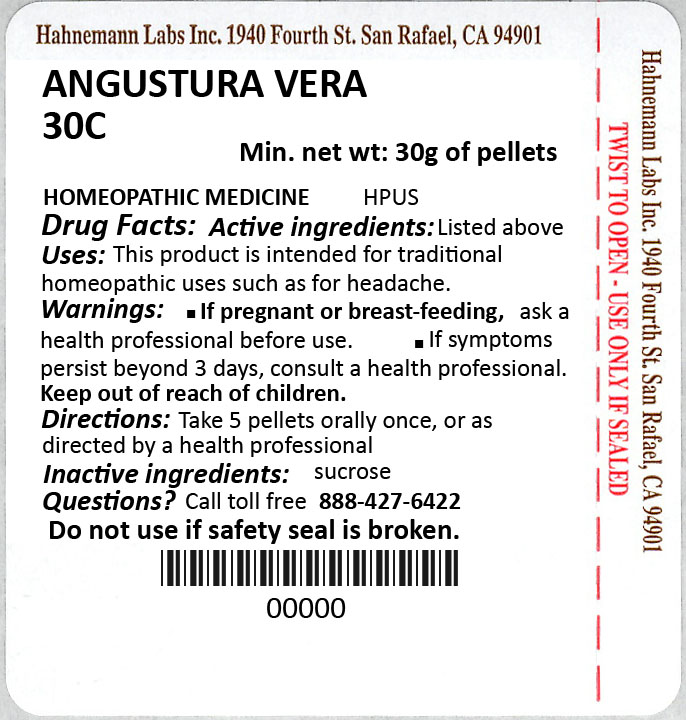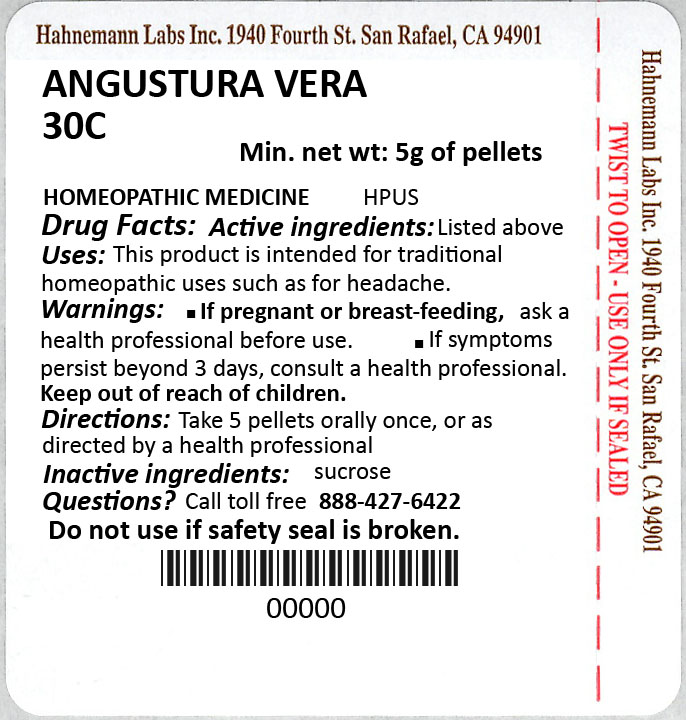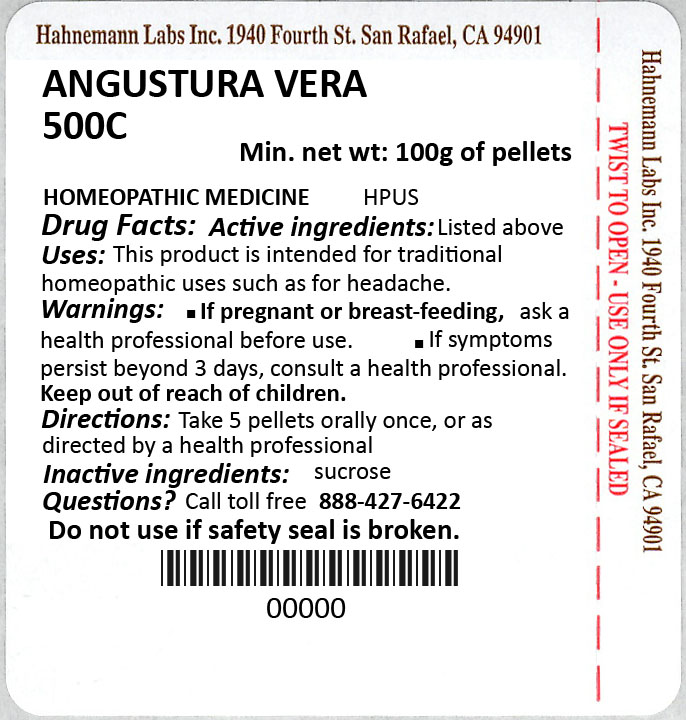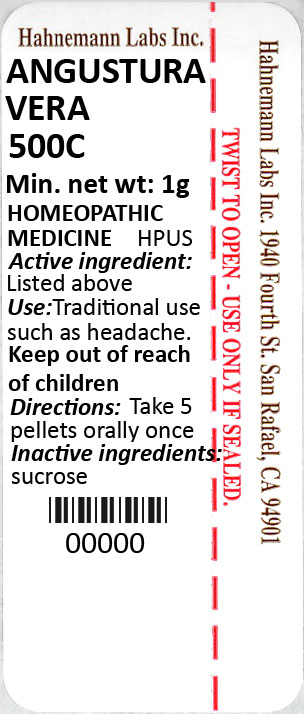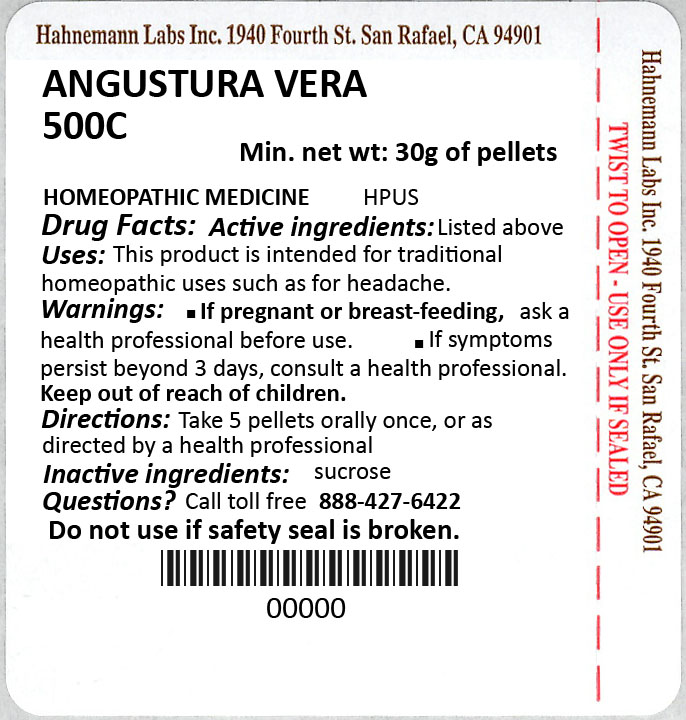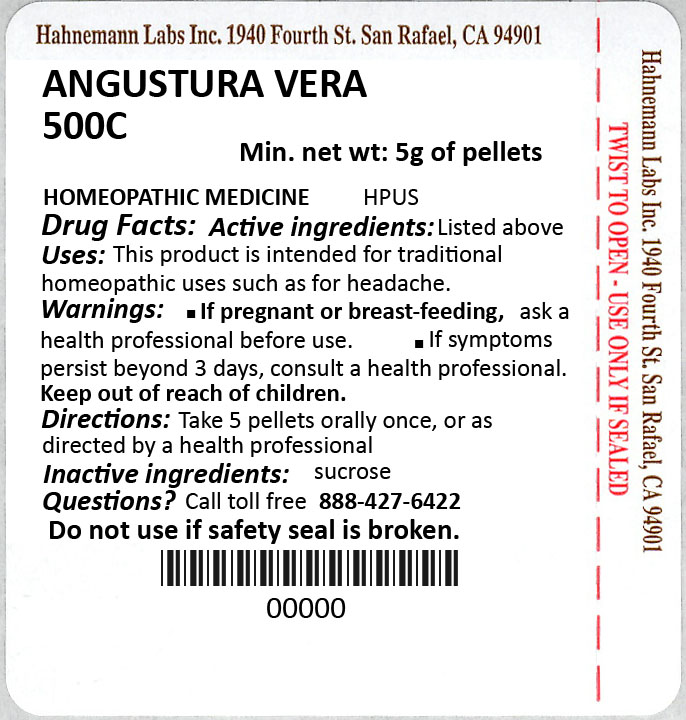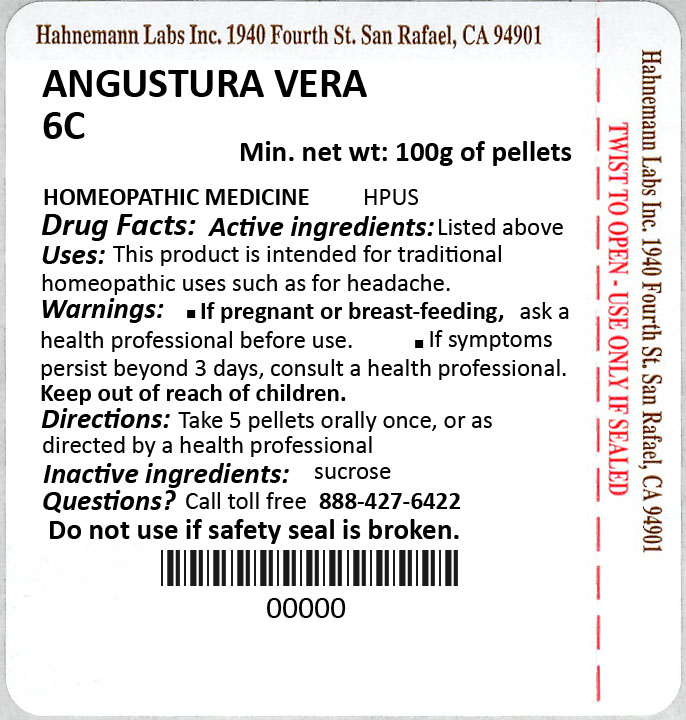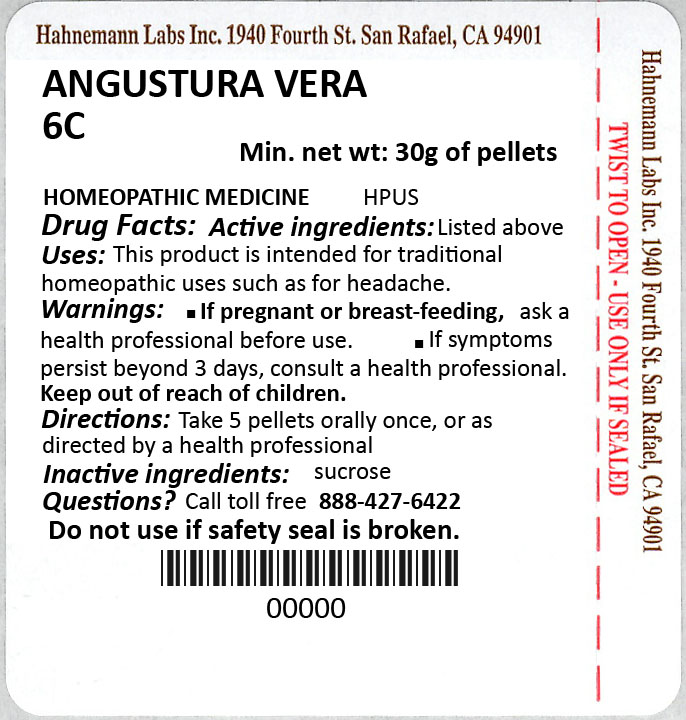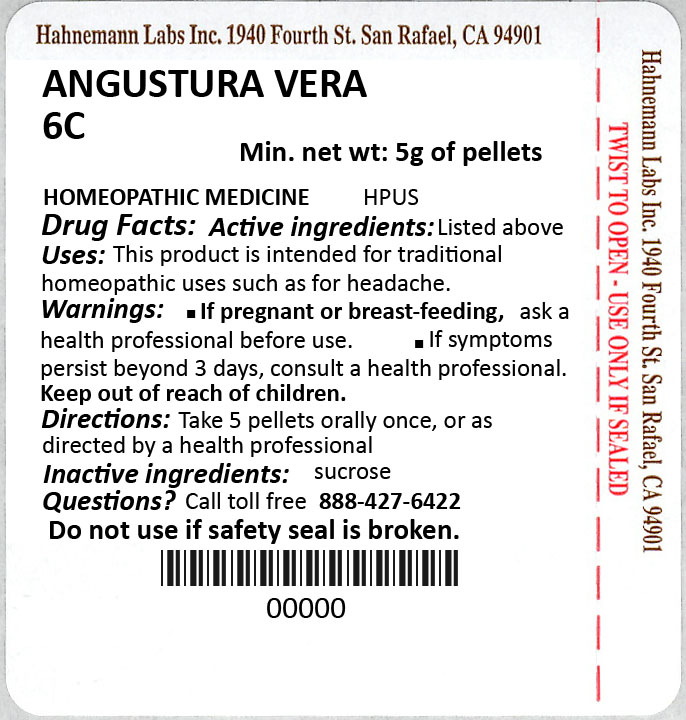 DRUG LABEL: Angustura Vera
NDC: 37662-3490 | Form: PELLET
Manufacturer: Hahnemann Laboratories, INC.
Category: homeopathic | Type: HUMAN OTC DRUG LABEL
Date: 20230630

ACTIVE INGREDIENTS: ANGOSTURA BARK 30 [hp_C]/1 1
INACTIVE INGREDIENTS: SUCROSE

PACKAGE LABEL

`